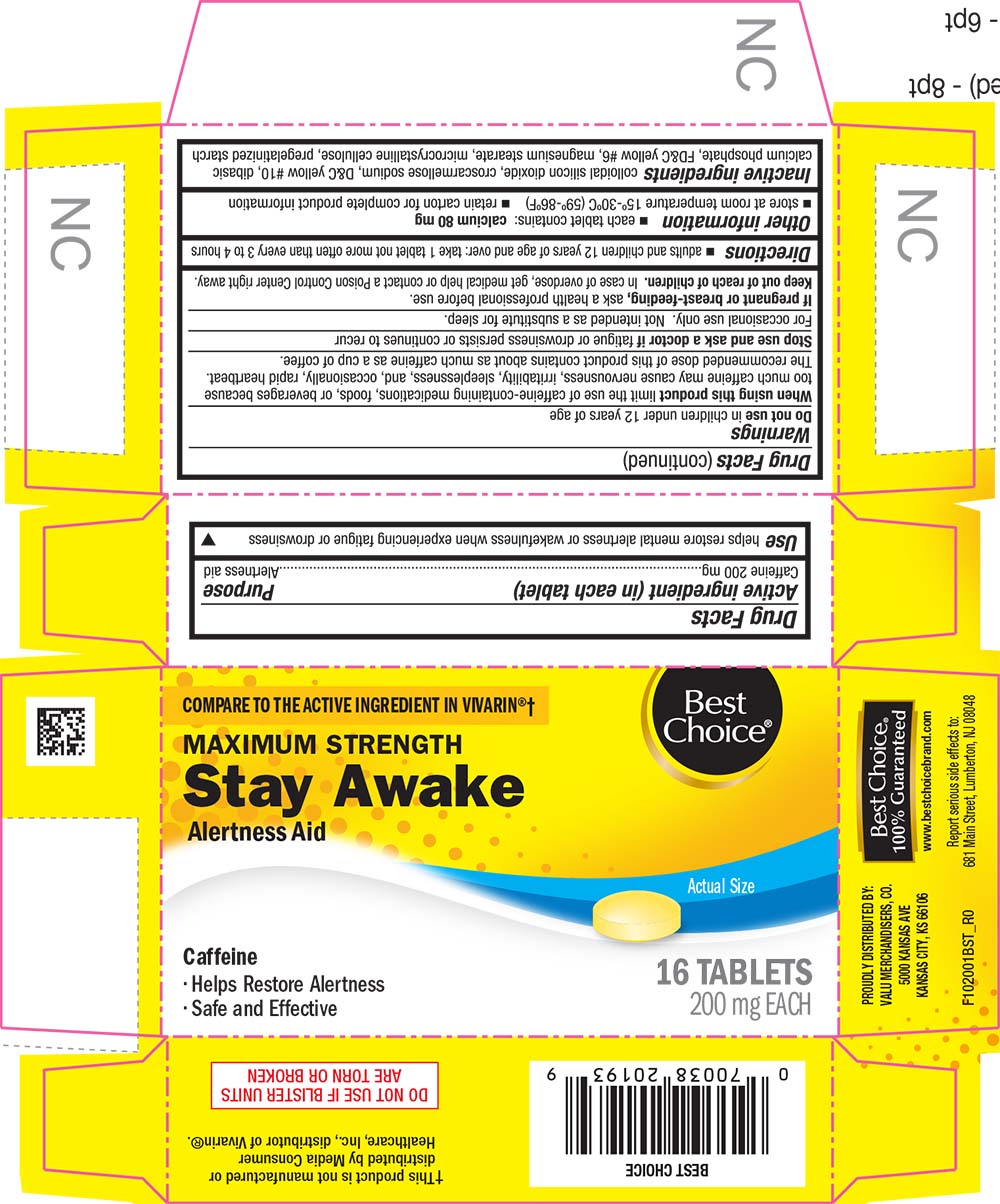 DRUG LABEL: Stay Awake
NDC: 63941-020 | Form: TABLET
Manufacturer: VALU MERCHANDISERS COMPANY
Category: otc | Type: HUMAN OTC DRUG LABEL
Date: 20251211

ACTIVE INGREDIENTS: CAFFEINE 200 mg/1 1
INACTIVE INGREDIENTS: SILICON DIOXIDE; CROSCARMELLOSE SODIUM; D&C YELLOW NO. 10; CALCIUM PHOSPHATE, DIBASIC, ANHYDROUS; FD&C YELLOW NO. 6; MAGNESIUM STEARATE; CELLULOSE, MICROCRYSTALLINE; STARCH, CORN

1020-BST-2021-1116

Drug Facts

Active ingredient (in each tablet)

Caffeine 200 mg

Purpose

Alertness aid

Use

helps restore mental alertness or wakefulness when experiencing fatigue or drowsiness

Warnings

Do not use in children under 12 years of age

When using this product limit the use of caffeine-containing medications, foods, or beverages because too much caffeine may cause nervousness, irritability, sleeplessness, and, occasionally, rapid heartbeat. The recommended dose of this product contains about as much caffeine as a cup of coffee.

Stop use and ask a doctor if fatigue or drowsiness persists or continues to recur

For occasional use only. Not intended as a substitute for sleep.

PREGNANCY OR BREAST FEEDING

If pregnant or breast-feeding, ask a health professional before use.

Keep out of reach of children. In case of overdose, get medical help or contact a Poison Control Center right away.

Directions

- adults and children 12 years of age and over: take 1 tablet not more often than every 3 to 4 hours

Other information

- each tablet contains: calcium 80 mg
- store at room temperature 15°-30°C (59°-86°F)
- retain carton for complete product information

Inactive ingredients

colloidal silicon dioxide, croscarmellose sodium, D&C yellow #10, dibasic calcium phosphate, FD&C yellow #6, magnesium stearate, microcrystalline cellulose, pregelatinized starch

PRINCIPAL DISPLAY PANEL

COMPARE TO THE ACTIVE INGREDIENT IN VIVARIN®†

Best Cjoice®

MAXIMUM STRENGTH

Stay Awake

Alertness Aid

Actual Size

Caffeine

• Helps Restore Alertness

• Safe and Effective

16 TABLETS

200 mg EACH